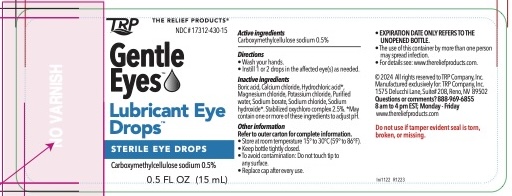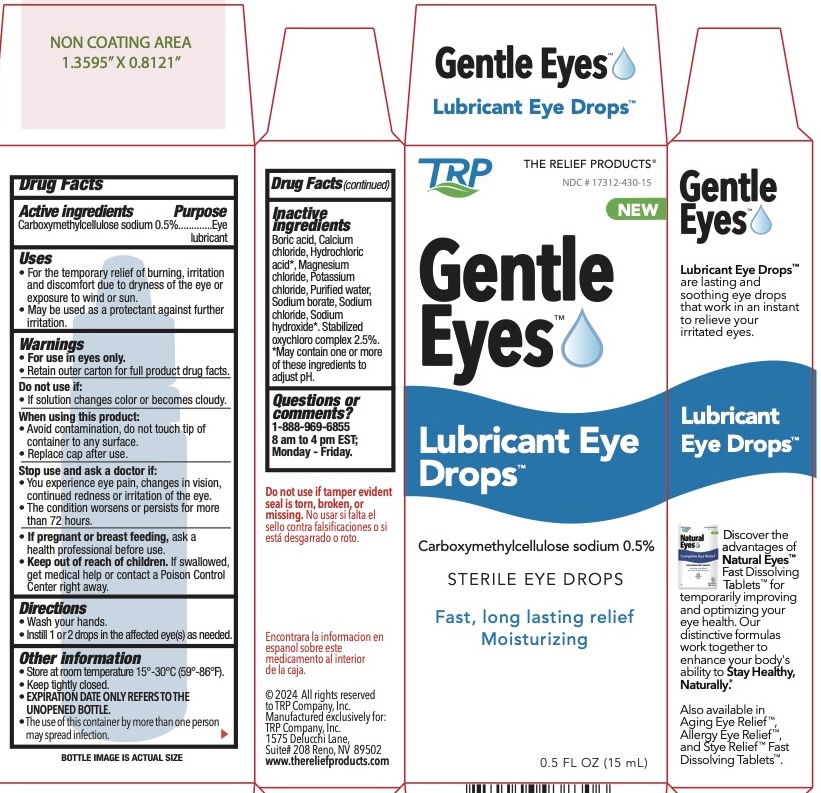 DRUG LABEL: Gentle Eyes Lubricant Eye Drops
NDC: 17312-430 | Form: SOLUTION/ DROPS
Manufacturer: TRP Company
Category: otc | Type: HUMAN OTC DRUG LABEL
Date: 20251215

ACTIVE INGREDIENTS: CARBOXYMETHYLCELLULOSE SODIUM 5 mg/1 mL
INACTIVE INGREDIENTS: BORIC ACID; CALCIUM CHLORIDE; MAGNESIUM CHLORIDE; POTASSIUM CHLORIDE; WATER; SODIUM CHLORITE; SODIUM BORATE; SODIUM CHLORIDE; HYDROCHLORIC ACID; SODIUM HYDROXIDE

Gentle Eyes Lubricant Eye Drops™

Active ingredient

Carboxymethylcellulose sodium 0.5%

Purpose

Eye lubricant

Uses

- For the temporary relief of burning, irritation, and discomfort due to dryness of the eye or exposure to wind or sun.
- May be used as a protectant against further irritation.

Warnings

- For use in eyes only.
- Retain outer carton for full product drug facts.

Stop use and ask a doctor if:

- You experience eye pain, changes in vision, continued redness or irritation of the eye.
- The condition worsens or persists for more than 72 hours.

Keep out of reach of children.If swallowed, get medical help or contact a Poison Control Center right awav.

Do not use

• If solution changes color or becomes cloudy.

When using this product:

- Avoid contamination, do not touch tip of container to any surface.
- Replace cap after use.

- If pregnant or breast feeding, ask a health professional before use.

Directions

- Wash your hands.
- Instill 1 or 2 drops in the affected eye(s) as needed.

Other information

- Store at room temperature 15°-30°C (59°-86°F).
- Keep tightly closed.
- EXPIRATION DATE ONLY REFERS TO THE UNOPENED BOTTLE.
- The use of this container by more than one person may spread infection.

Inactive ingredients

Boric acid, Calcium| chloride, Hydrochloric acid*, Magnesium chloride, Potassium chloride, Purified water, Sodium borate, Sodium chloride, Sodium hydroxide*. Stabilized axychloro complex 2.5%.

*May contain one or more of these ingredients to adjust pH.

Questions or comments?

1-888-969-6855

8 am to 4 pm EST;

Monday - Friday.